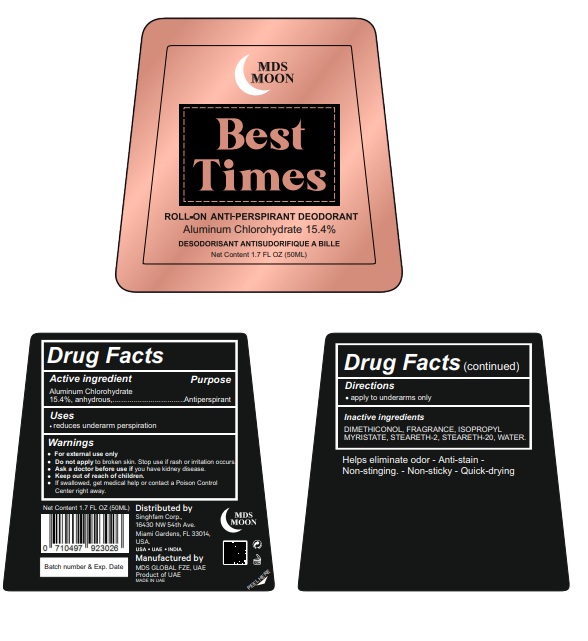 DRUG LABEL: MDS Roll-On Anti-Perspirant
NDC: 87119-001 | Form: CREAM
Manufacturer: MDS GLOBAL FZE
Category: otc | Type: HUMAN OTC DRUG LABEL
Date: 20251110

ACTIVE INGREDIENTS: ALUMINUM CHLOROHYDRATE ANHYDROUS 15.4 g/100 mL
INACTIVE INGREDIENTS: ISOPROPYL MYRISTATE; STEARETH-2; STEARETH-20; WATER; DIMETHICONE, UNSPECIFIED

Active ingredient

Aluminum Chlorohydrate, 15.4 % anhydrous

Purpose

Anti-Perspirant Deodorant

Uses

reduces underarm perspiration

Warnings

- For external use only
- Do not apply to broken skin. Stop use if rash or irritation occurs.
- Ask a doctor before use if you have kidney disease.
- Keep out of reach of children.
- If swallowed, get medical help or contact a Poison Control Center right away.

Directions

- apply to underarms only

Inactive ingredients

DIMETHICONOL, FRAGRANCE, ISOPROPYL MYRISTATE, STEARETH-2, STEARETH-20, WATER.

Other information

Helps eliminate odor - Anti-stain -Non-stinging. - Non-sticky - Quick-drying